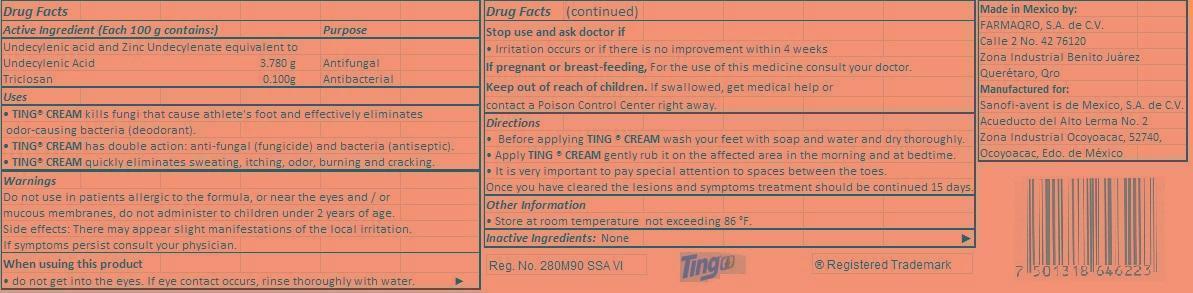 DRUG LABEL: TING
NDC: 51769-003 | Form: CREAM
Manufacturer: ALL NATURAL DYNAMICS
Category: otc | Type: HUMAN OTC DRUG LABEL
Date: 20130315

ACTIVE INGREDIENTS: Undecylenic acid 3.780 g/100 g; TRICLOSAN .100 g/100 g
INACTIVE INGREDIENTS: TITANIUM DIOXIDE; Petrolatum

Ting Cream for athletes foot

Purpose

Undecylenic Acid Antifungal

Triclosan Antibacterial

Keep out of reach of children.

If swallowed, get medical help or contact a Poison Control Center right away.

Uses

• TING® CREAM kills fungi that cause athlete's foot and effectively eliminates odor-causing bacteria (deodorant).

• TING® CREAM has double action: anti-fungal (fungicide) and bacteria (antiseptic).

• TING® CREAM quickly eliminates sweating, itching, odor, burning and cracking.

Warnings

Do not use in patients allergic to the formula, or near the eyes and/or mucous membranes, do not administer to children under 2 years of age.

Side effects: There may appear slight manifestations of the local irritation.

If symptoms persist consult your physician.

Directions

• Before applying TING ® CREAM wash your feet with soap and water and dry thoroughly.

• Apply TING ® CREAM gently rub it on the affected area in the morning and at bedtime.

• It is very important to pay special attention to spaces between the toes.

Once you have cleared the lesions and symptoms treatment should be continued 15 days.

Inactive ingredient

None